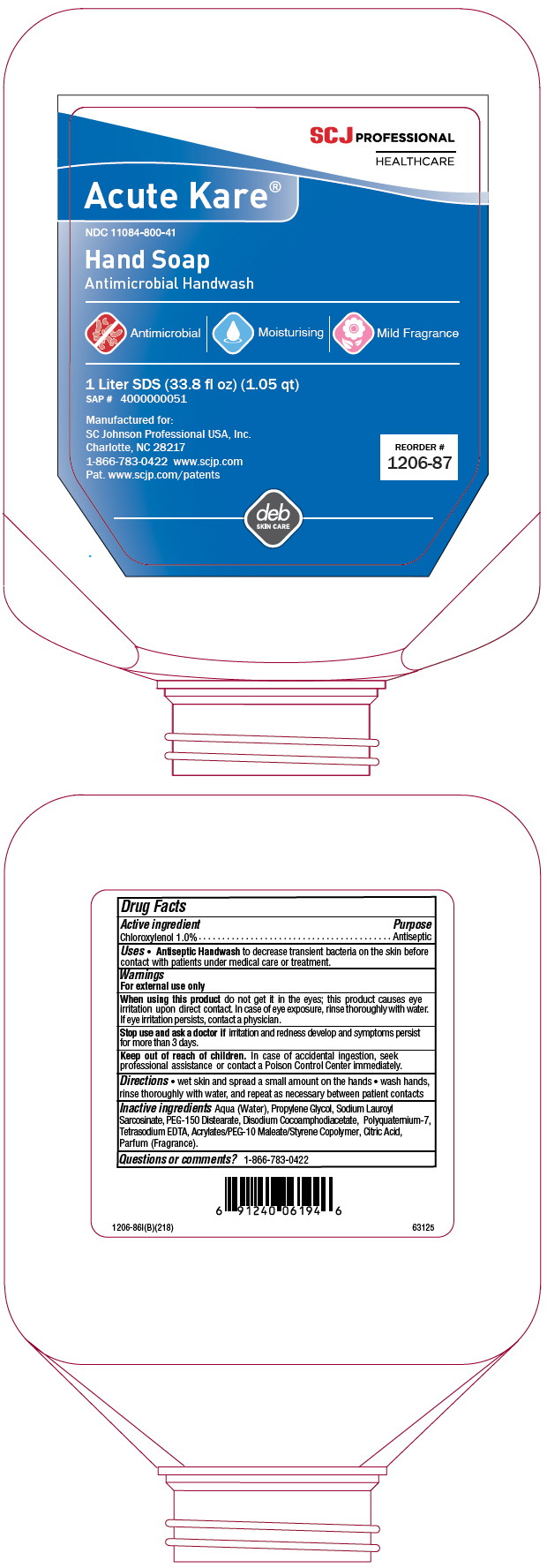 DRUG LABEL: Acute-Kare
NDC: 11084-800 | Form: SOAP
Manufacturer: SC Johnson Professional USA, Inc.
Category: otc | Type: HUMAN OTC DRUG LABEL
Date: 20241217

ACTIVE INGREDIENTS: CHLOROXYLENOL 1 g/100 mL
INACTIVE INGREDIENTS: WATER; PROPYLENE GLYCOL; SODIUM LAUROYL SARCOSINATE; PEG-150 DISTEARATE; DISODIUM COCOAMPHODIACETATE; POLYQUATERNIUM-7 (70/30 ACRYLAMIDE/DADMAC; 1600000 MW); EDETATE SODIUM; METHACRYLATE/METHOXY PEG-10 MALEATE/STYRENE COPOLYMER; CITRIC ACID MONOHYDRATE

Acute-Kare®
Healthcare Personnel Handwash

Drug Facts

Active ingredient

Chloroxylenol 1.0%

Purpose

Antiseptic

Uses

- Antiseptic Handwash to decrease transient bacteria on the skin before contact with patients under medical care or treatment.

Warnings

For external use only

When using this product do not get it in the eyes; this product causes eye irritation upon direct contact. In case of eye exposure, rinse thoroughly with water. If eye irritation persists, contact a physician.

Stop use and ask a doctor if irritation and redness develop and symptoms persist for more than 3 days.

Keep out of reach of children. In case of accidental ingestion, seek professional assistance or contact a Poison Control Center immediately.

Directions

- wet skin and spread a small amount on the hands
- wash hands, rinse thoroughly with water, and repeat as necessary between patient contacts

Inactive ingredients

Aqua (Water), Propylene Glycol, Sodium Lauroyl Sarcosinate, PEG-150 Distearate, Disodium Cocoamphodiacetate, Polyquaternium-7, Tetrasodium EDTA, Acrylates/PEG-10 Maleate/Styrene Copolymer, Citric Acid, Parfum (Fragrance).

Questions or comments?

1-866-783-0422

PRINCIPAL DISPLAY PANEL - 1 Liter Bottle Label

SCJ PROFESSIONAL
HEALTHCARE

Acute Kare®

NDC 11084-800-41

Hand Soap
Antimicrobial Handwash

Antimicrobial | Moisturising | Mild Fragrance

1 Liter SDS (33.8 fl oz) (1.05 qt)
SAP # 4000000051

Manufactured for:
SC Johnson Professional USA, Inc.
Charlotte, NC 28217
1-866-783-0422 www.scjp.com
Pat. www.scjp.com/patents

REORDER #
1206-87

deb
SKIN CARE